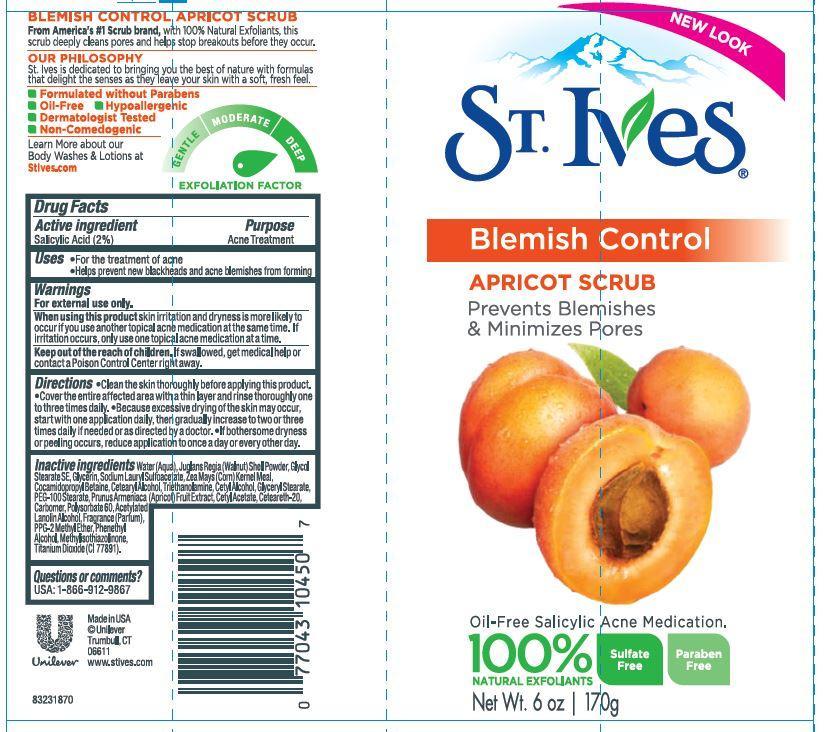 DRUG LABEL: St. Ives
NDC: 64942-1245 | Form: EMULSION
Manufacturer: CONOPCO Inc. d/b/a Unilever
Category: otc | Type: HUMAN OTC DRUG LABEL
Date: 20131105

ACTIVE INGREDIENTS: Salicylic Acid 0.02 g/1 g
INACTIVE INGREDIENTS: WATER; JUGLANS REGIA SHELL; Glycerin; SODIUM LAURYL SULFOACETATE; GLYCERYL MONOSTEARATE; CORN GRAIN; COCAMIDOPROPYL BETAINE; CETOSTEARYL ALCOHOL; TROLAMINE; CETYL ALCOHOL; PEG-100 STEARATE; APRICOT; CETYL ACETATE; POLYOXYL 20 CETOSTEARYL ETHER; TITANIUM DIOXIDE; POLYSORBATE 60; PHENYLETHYL ALCOHOL; METHYLISOTHIAZOLINONE; ACETYLATED LANOLIN ALCOHOLS; PPG-2 METHYL ETHER

St. Ives Blemish and Blackhead Control Apricot Scrub

Active ingredient
Salicylic Acid (2%)

Purpose
Acne Treatment

Uses

· For the treatment of acne

· Helps prevent new blackheads and acne blemishes from forming

Warnings
For external use only.

When using this product, skin irritation and dryness is more likely to occur if you use another topical acne medication at the same time. If irritation occurs, only use one topical acne medication at a time.

Keep out of reach of children. If swallowed, get medical help or contact a Poison Control Center right away.

Directions

· Clean the skin thoroughly before applying this product.

· Cover the entire affected area with a thin layer and rinse thoroughly one to three times daily.

· Because excessive drying of the skin may occur, start with one application daily, then gradually increase to two or three times daily if needed or as directed by a doctor.

· If bothersome dryness or peeling occurs, reduce application to once a day or every other day.

Inactive ingredients

Water (Aqua), Juglans Regia (Walnut) Shell Powder, Glycol Stearate SE, Glycerin, Sodium Lauryl Sulfoacetate, Zea Mays (Corn) Kernel Meal, Cocamidopropyl Betaine, Cetearyl Alcohol, Triethanolamine, Cetyl Alcohol, Glyceryl Stearate, PEG-100 Stearate, Prunus Armeniaca (Apricot) Fruit Extract, Cetyl Acetate, Ceteareth-20, Carbomer, Polysorbate 60, Acetylated Lanolin Alcohol, Fragrance (Parfum), PPG-2 Methyl Ether, Phenethyl Alcohol, Methylisothiazolinone, Titanium Dioxide (CI 77891).

Questions or comments?
USA: 1-866-912-9867